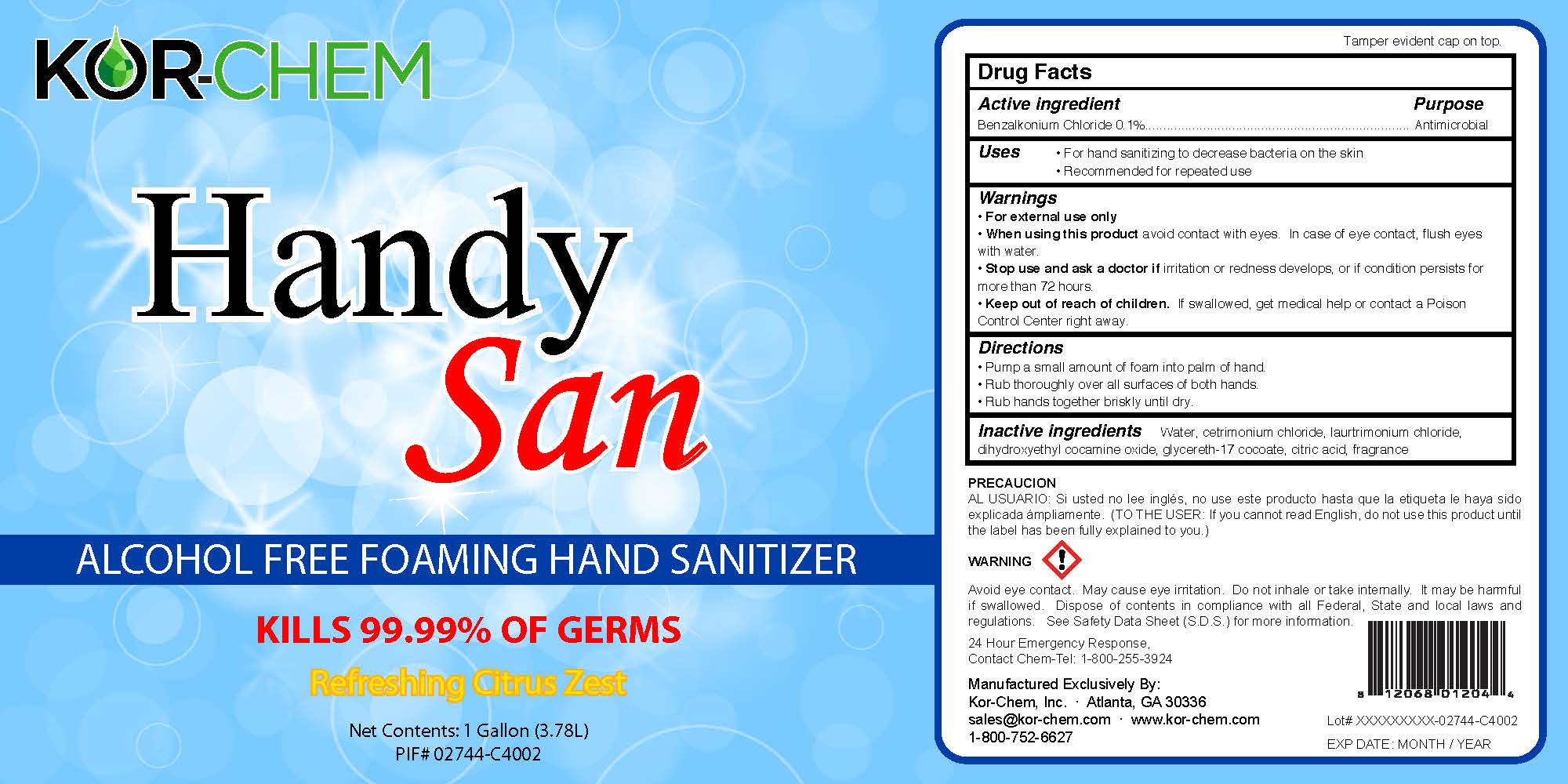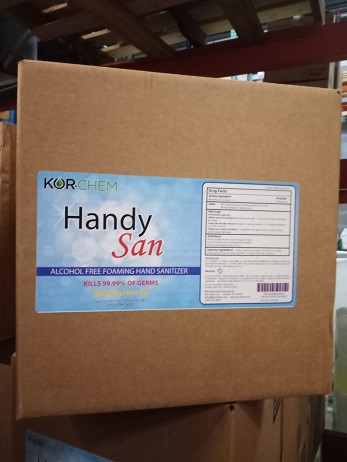 DRUG LABEL: Handy San
NDC: 62881-003 | Form: LIQUID
Manufacturer: Kor-Chem, Inc
Category: otc | Type: HUMAN OTC DRUG LABEL
Date: 20220131

ACTIVE INGREDIENTS: BENZALKONIUM CHLORIDE 0.2 g/100 g
INACTIVE INGREDIENTS: FRAGRANCE LEMON ORC2001060 0.1 g/100 g; RECOMBINANT FRAGMENT HUMAN SURFACTANT PROTEIN-D HOMOTRIMER 10 g/100 g; WATER 89.7 g/100 g

Handy San

Alcohol free foaming hand sanitizer

Purified water 89.7%

Macat N-10X 10%

Nobac BXK NF/USP 0.2%

Fragrance 0.1%

Active Ingredient(s)

Nobac BZK NF/USP, 0.2 percent

Handy San

Antiseptic, Hand Sanitizer

Use

Hand Sanitizer to help reduce bacteria that potentially can cause disease. For use when soap and water are not available.

Warnings

For external use only. Flammable. Keep away from heat or flame

Do not use

- in children less than 2 months of age
- on open skin wounds

When using this product keep out of eyes, ears, and mouth. In case of contact with eyes, rinse eyes thoroughly with water.
Stop use and ask a doctor if irritation or rash occurs. These may be signs of a serious condition.
Keep out of reach of children. If swallowed, get medical help or contact a Poison Control Center right away.

Stop use and ask a doctor if irritation or rash occurs. These may be signs of a serious condition.

Keep out of reach of children. If swallowed, get medical help or contact a Poison Control Center right away.

Directions

- Place enough product on hands to cover all surfaces. Rub hands together until dry.
- Supervise children under 6 years of age when using this product to avoid swallowing.

Other information

- Store between 15-30C (59-86F)
- Avoid freezing and excessive heat above 40C (104F)

Inactive ingredients

Nacat N-10X 10%

Fragrance 0.10%

Purified water USP 89.7%

02744-C4002 - HandySan-4x1gal BOTTLE LABEL - 5x10 GHS.jpg